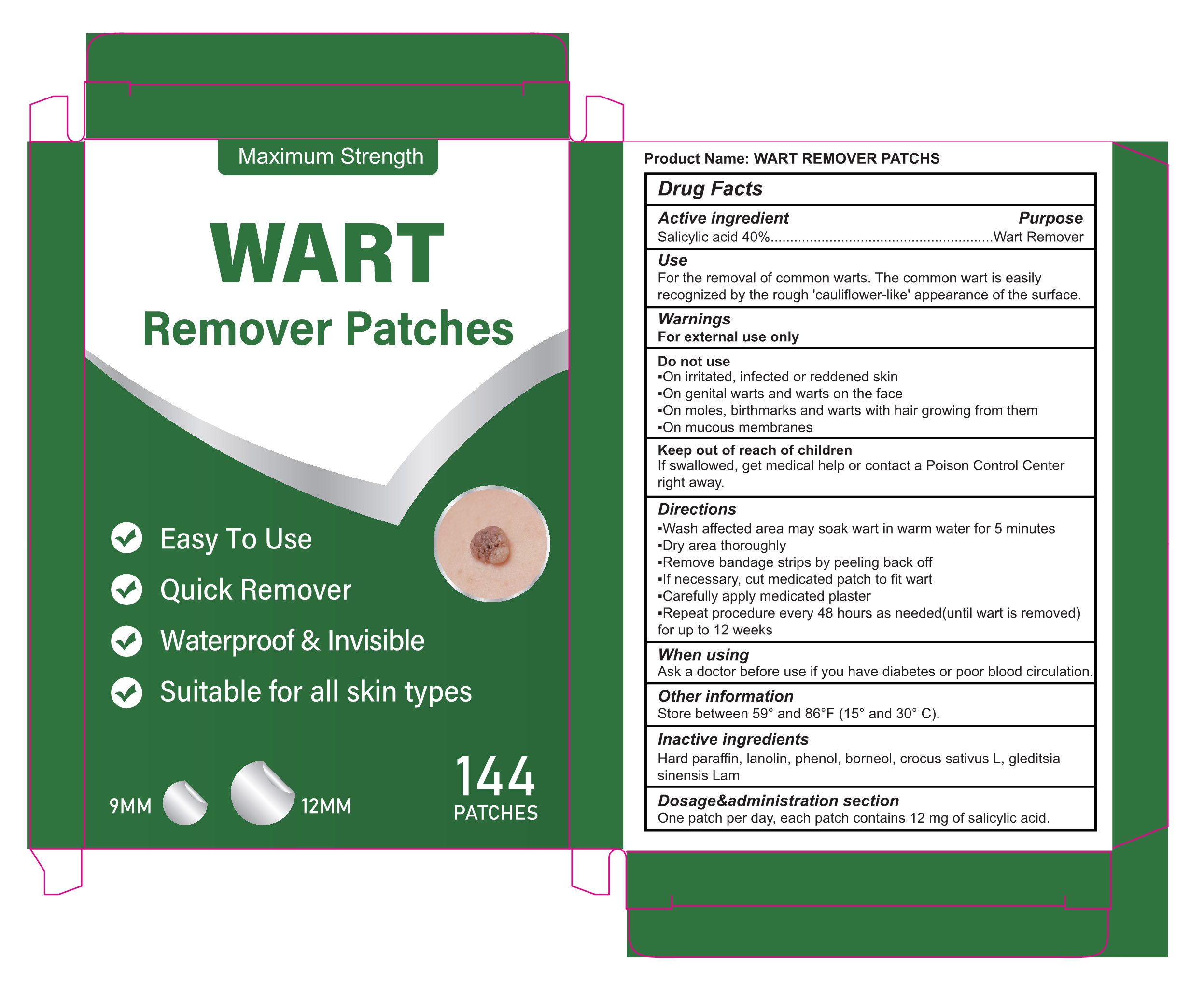 DRUG LABEL: WART Remover
NDC: 87255-004 | Form: PATCH
Manufacturer: Shenzhen Mengyue Technology Co., Ltd.
Category: otc | Type: HUMAN OTC DRUG LABEL
Date: 20251201

ACTIVE INGREDIENTS: SALICYLIC ACID 40 g/100 1
INACTIVE INGREDIENTS: PHENOL; PARAFFIN; GLEDITSIA SINENSIS WHOLE; CROCUS SATIVUS WHOLE; BORNEOL; LANOLIN

004 WART Remover Patches

ACTIVE INGREDIENT

Salicylic Acid 40%

PURPOSE

Wart Remover

Use

For the removal of common warts. The common wart is easily recognized by the rough 'cauliflower-like' appearance of the surface.

Warnings

For external use only

Do not use

•On irritated, infected or reddened skin

•On genital warts and warts on the face

•On moles, birthmarks and warts with hair growing from them

•On mucous membranes

When using

Ask a doctor before use if you have diabetes or poor blood circulation.

Keep out of reach of children

If swallowed, get medical help or contact a Poison Control Center right away.

Directions

·Wash affected area may soak wart in warm water for 5 minutes

·Dry area thoroughly

·Remove bandage strips by peeling back off

·If necessary, cut medicated patch to fit wart

·Carefully apply medicated plaster

·Repeat procedure every 48 hours as needed(until wart is removed) for up to 12 weeks

Other information

Store between 59° and 86°F (15° and 30° C).

INACTIVE INGREDIENT

Inactive ingredientsHard paraffin, lanolin, phenol, borneol, crocus sativus L, gleditsia sinensis Lam

Dosage&administration section

One patch per day, each patch contains 12 mg of salicylic acid.